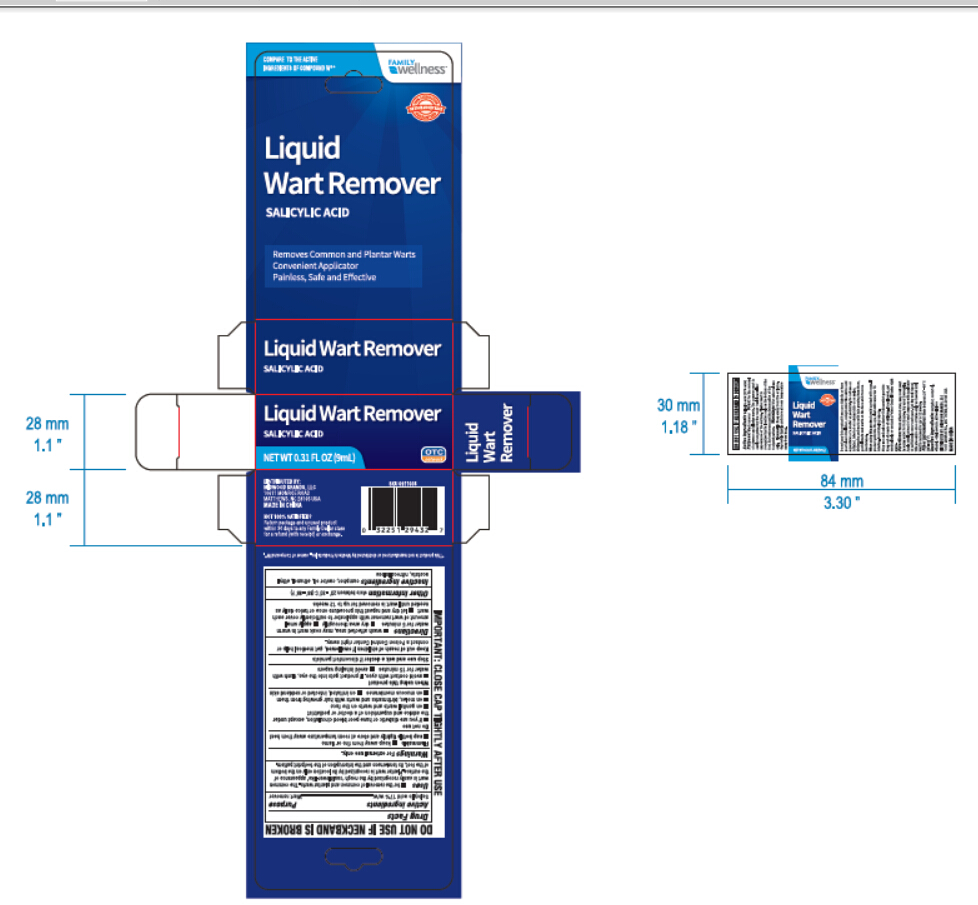 DRUG LABEL: Family Wellness
NDC: 58194-600 | Form: LIQUID
Manufacturer: Shanghai Weierya Daily Chemicals Factory
Category: otc | Type: HUMAN OTC DRUG LABEL
Date: 20170625

ACTIVE INGREDIENTS: SALICYLIC ACID 17 g/100 mL
INACTIVE INGREDIENTS: CAMPHOR (SYNTHETIC); CASTOR OIL; ALCOHOL; ETHYL ACETATE; PYROXYLIN

Drug Facts

Active ingredients

Salicylic acid 17% w/w

Purpose

Wart remover

INDICATIONS AND USAGE

Uses •for the removal of common and plantar warts. The common

wart is easily recognized by the 'cauliflower-like' appearance of

the surface. Plantar wart is recognized by its location only on the bottom

of the foot, its tenderness and the interruption of the foot pattern.

Warnings For external use only.

Flammable •keep away from fire or flame

•cap bottle tightly and store at room temperature away from heat

Do not use

•if you are diabetic or have poor blood circulation, except under

the advice and supervision of a doctor or a podiatrist

•on genital warts and warts on the face

•on moles, birthmarks and warts with hair growing from them

•on mucuous membranes •on irritated, infected or reddend skin

When using this product

•avoid contact with eyes. If product gets into the eye, flush with

water for 15 minutes •avoid inhaling vapors

Stop use and ask a doctor if discomfort persists.

Keep out of reach of children If swallowed, get medical help or

contact a Poison Control Center right away.

DOSAGE AND ADMINISTRATION

Directions •wash affected area, may soak wart in warm

water for 5 minutes •dry area thoroughly •apply small

amount of wart remover with applicator to sufficiently cover each

wart •let dry and repeat this procedure once or twice daily as

needed until wart is removed for up to 12 weeks

Other information store between 20° - 30° C (68° - 86° F)

Inactive ingredients camphor, castor oil, ethanol, ethyl

acetate, nitrocellulose